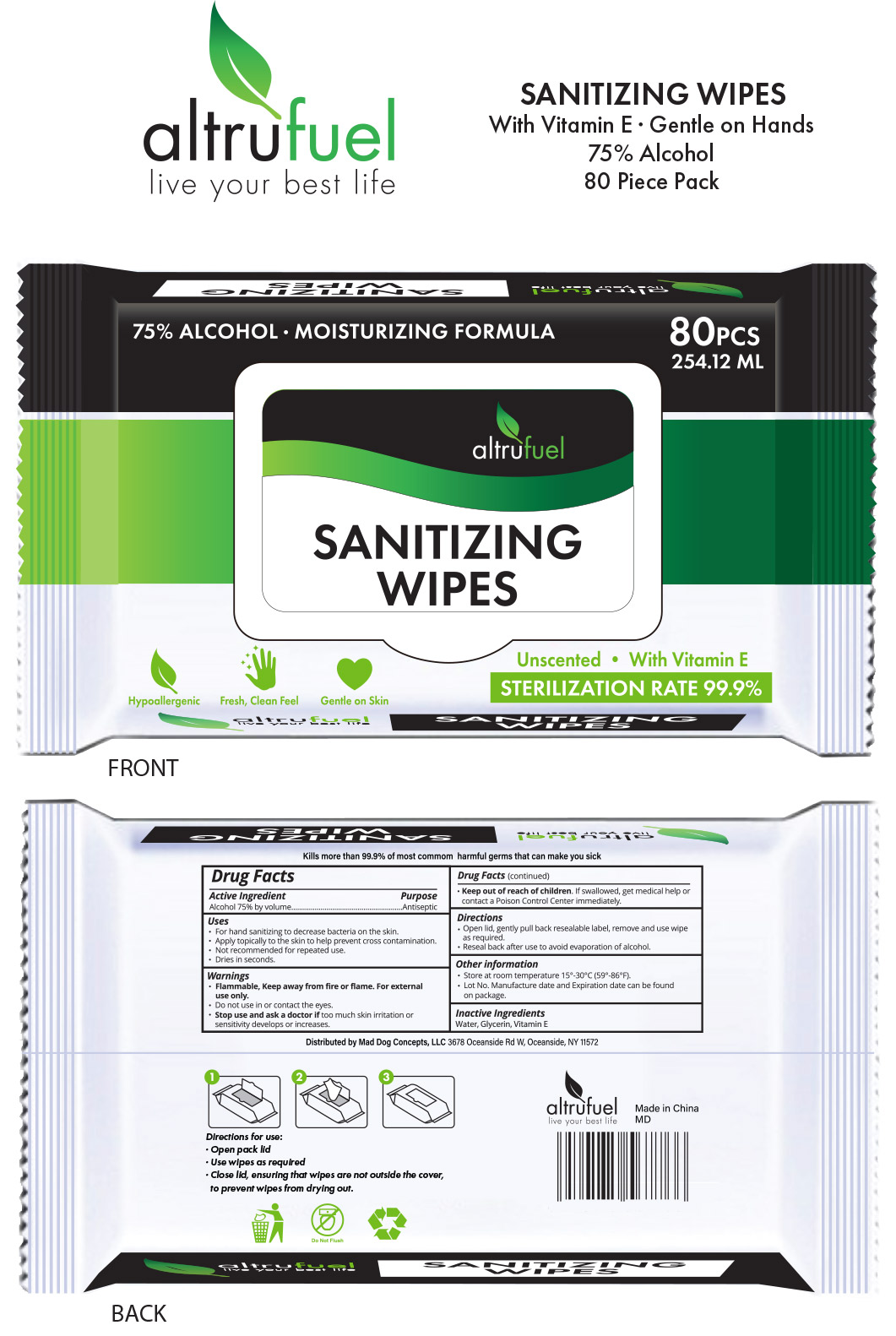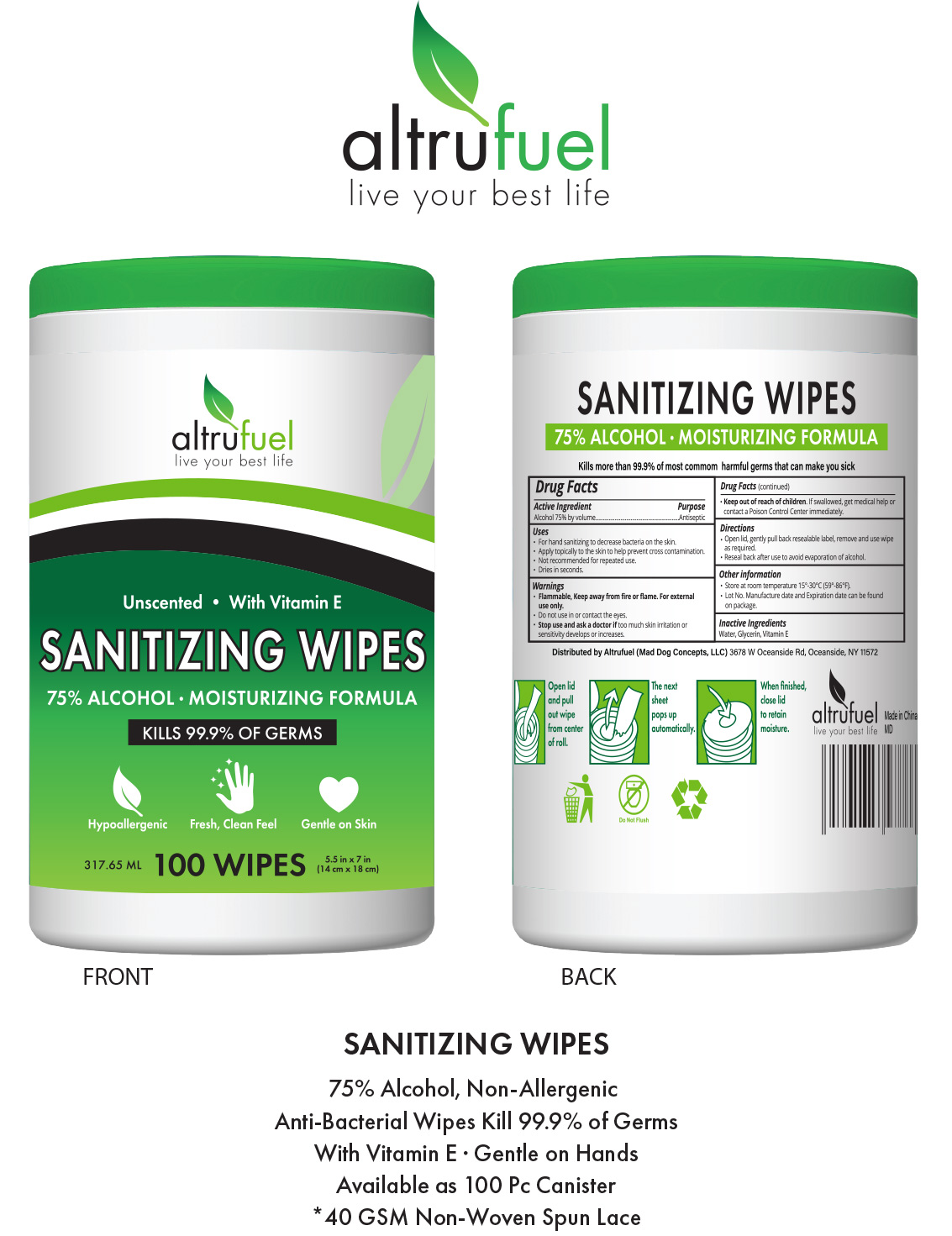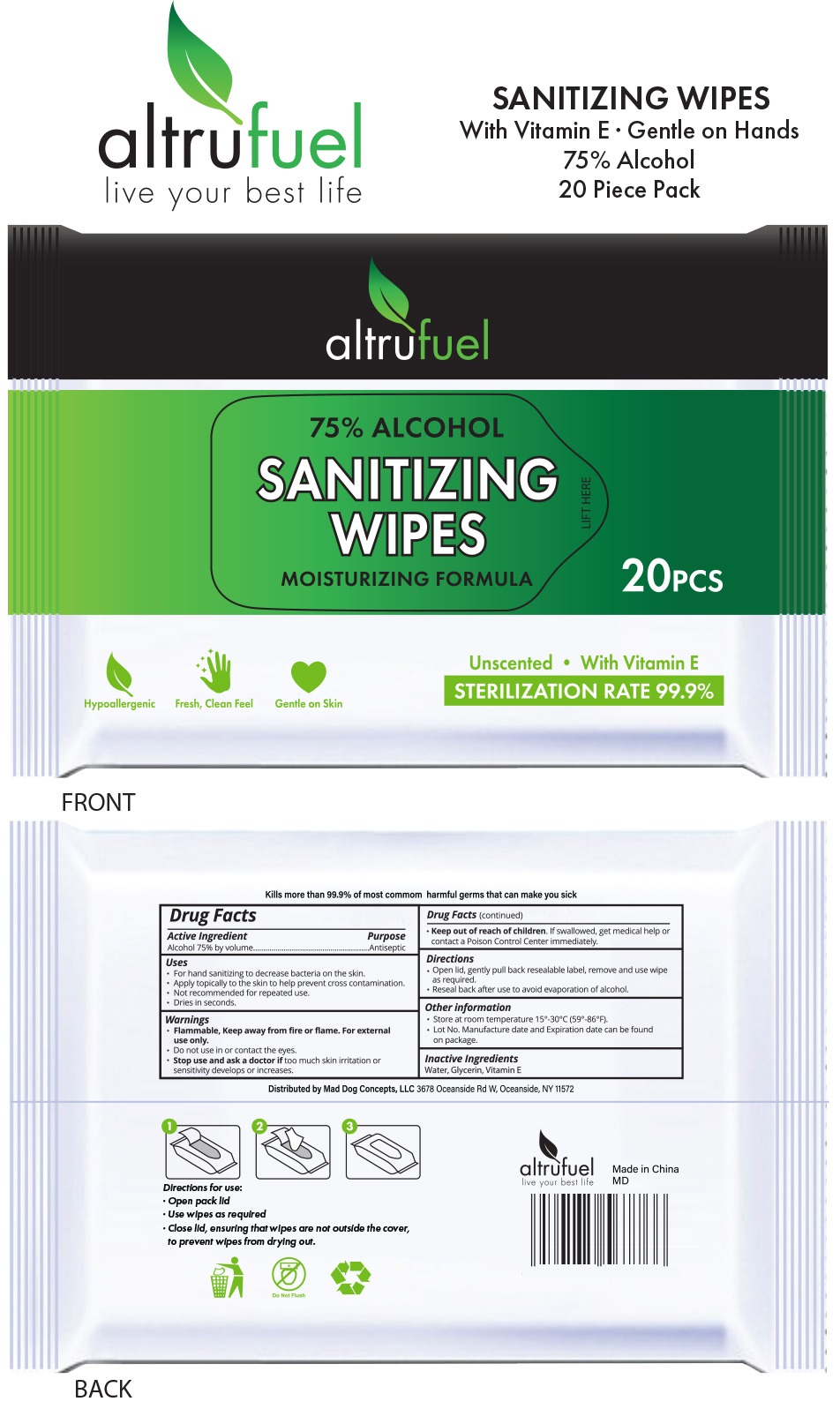 DRUG LABEL: Altrufuel ALCOHOL WIPES
NDC: 75421-002 | Form: CLOTH
Manufacturer: Mad Dog Concepts, LLC
Category: otc | Type: HUMAN OTC DRUG LABEL
Date: 20200806

ACTIVE INGREDIENTS: ALCOHOL 0.75 mL/1 mL
INACTIVE INGREDIENTS: WATER; GLYCERIN; .ALPHA.-TOCOPHEROL

Altrufuel ALCOHOL WIPES

Active Ingredient

Alcohol 75% by volume

Purpose

Antiseptic

Use

- For hand sanitizing to decrease bacteria on the skin.
- Apply topically to the skin to help prevent cross contamination.
- Not recommended for repeated use.
- Dries in seconds.

Warnings

Flammable. Keep from fire or flame.

For external use only

Do not use

in or contact the eyes.

Stop use and ask a doctor if

too much skin irritation or sensitivity develops or increases.

Keep out of reach of children.

Iif swallowed, get medical help or contact a Poison Control Center immediately.

Directions

- Open lid, gently pull back resealable label, remove and use wipe as required.
- Reseal back after use to avoid evaporation of alcohol.

Other Information

- Store at room temperature 15°-30°C (59°-86°F).
- Lot No. Manufacture date and Expiration date can be found on package.

Inactive Ingredients

Water, Glycerin, Vitamin E